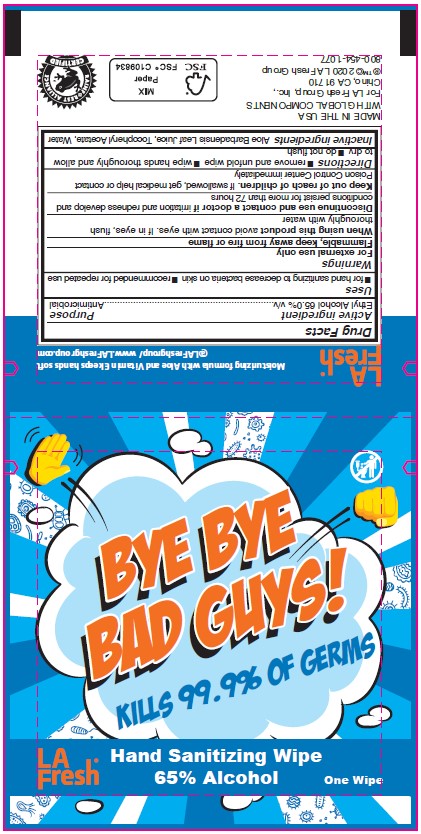 DRUG LABEL: LA Fresh Hand Sanitizing Wipe
NDC: 64709-150 | Form: CLOTH
Manufacturer: Diamond Wipes International, Inc
Category: otc | Type: HUMAN OTC DRUG LABEL
Date: 20201030

ACTIVE INGREDIENTS: ALCOHOL 65 g/100 g
INACTIVE INGREDIENTS: ALOE VERA LEAF; .ALPHA.-TOCOPHEROL ACETATE; WATER

LA Fresh Hand Sanitizing Wipe

Active ingredient

Ethyl Alcohol 65.0%

Purpose

Antimicrobial

Use

• for hand sanitizing to decrease bacteria on skin • recommended for repeated use

Warnings

For external use only

Flammable, keep away from fire or flame

When using this product

avoid contact with eyes. If in eyes, flush thoroughly with water

Discontinue use and contact a doctor

if irritation and redness develop and
conditions persist for more than 72 hours

Keep out of reach of children

If swallowed, get medical help or contact a Poison Control Center immediately

Directions

• remove and unfold wipe

• wipe hands thoroughly and allow to dry

• do not flush

Inactive ingredients

Aloe Barbadensis Leaf Juice, Tocopheryl Acetate, Water

Label

BYE BYE BAD GUYS!

KILLS 99.9% OF GERMS

LA Fresh

Hand Sanitizing Wipe

65% Alcohol

One Wipe

Moisturizing formula with Aloe and Vitamin E keeps hands soft

@LAFreshgroup/www.LAFreshgroup.com

MADE IN THE USA

WITH GLOBAL CPMPONENTS

For LA Fresh Group, Inc.,

Chino, CA 91710

®TM© 2020 LA Fresh Group

800-454-1077

FSC FSC C109834 MIX Paper

RAINFOREST ALLIANCE CERTIFIED